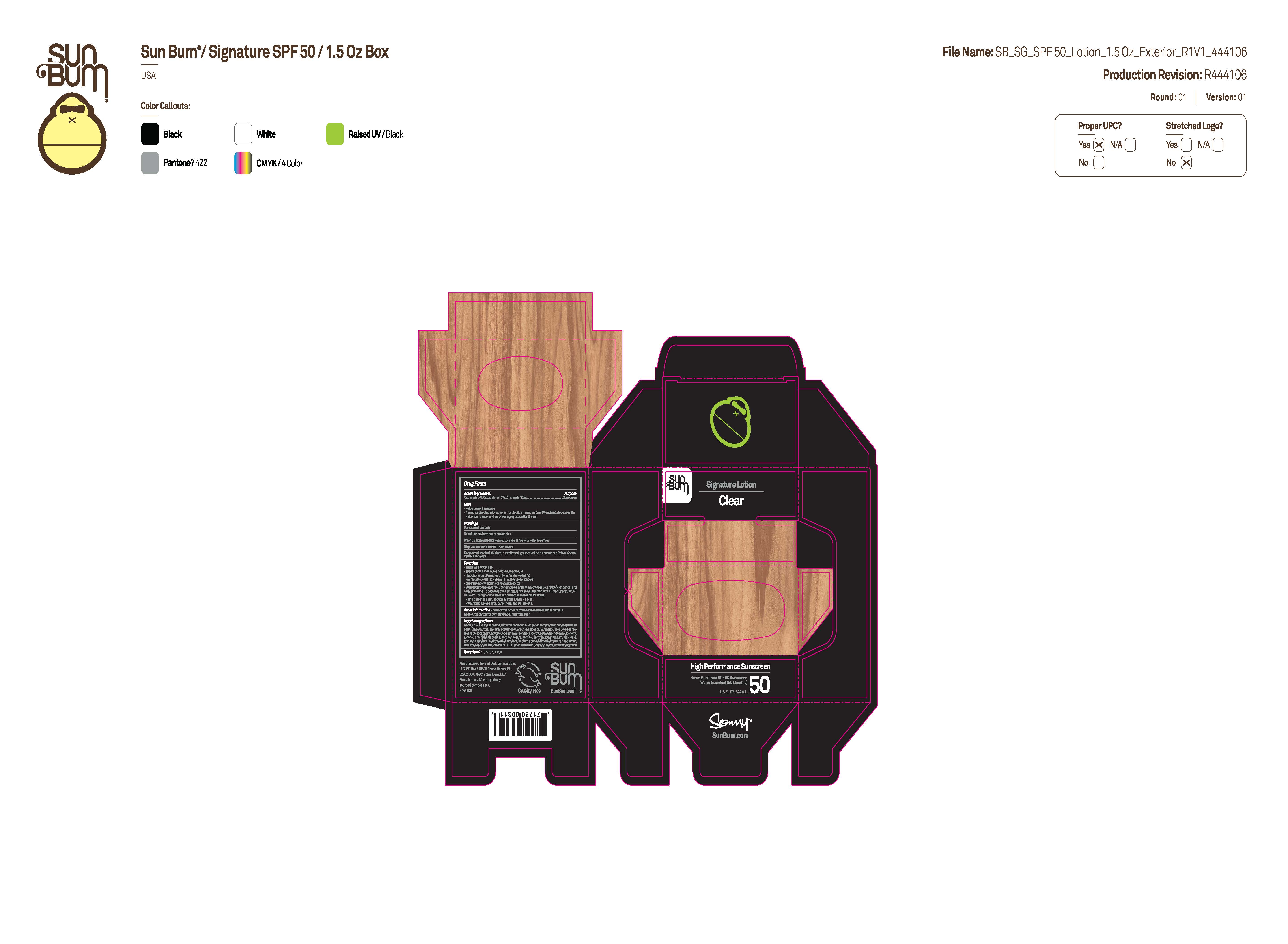 DRUG LABEL: Sun Bum Signature Clear High Performance Sunscreen Broad Spectrum SPF 50 1.5 OZ
NDC: 69039-763 | Form: LOTION
Manufacturer: Sun Bum, LLC
Category: otc | Type: HUMAN OTC DRUG LABEL
Date: 20250818

ACTIVE INGREDIENTS: ZINC OXIDE 100 mg/1 mL; OCTISALATE 50 mg/1 mL; OCTOCRYLENE 100 mg/1 mL
INACTIVE INGREDIENTS: GLYCERIN; OLEIC ACID; ALOE BARBADENSIS LEAF JUICE; C12-15 ALKYL BENZOATE; .ALPHA.-TOCOPHEROL ACETATE; SORBITOL; EDETATE DISODIUM; ASCORBYL PALMITATE; ARACHIDYL ALCOHOL; SORBITAN OLEATE; TRIMETHYLPENTANEDIOL/ADIPIC ACID/GLYCERIN CROSSPOLYMER (25000 MPA.S); BEHENYL ALCOHOL; PHENOXYETHANOL; BEESWAX; GLYCERYL CAPRYLATE; SODIUM HYALURONATE; ETHYLHEXYLGLYCERIN; HYDROXYETHYL ACRYLATE/SODIUM ACRYLOYLDIMETHYL TAURATE COPOLYMER (45000 MPA.S AT 1%); BUTYROSPERMUM PARKII (SHEA) BUTTER; LECITHIN, SUNFLOWER; CAPRYLYL GLYCOL; ARACHIDYL GLUCOSIDE; WATER; POLYESTER-8 (1400 MW, CYANODIPHENYLPROPENOYL CAPPED); XANTHAN GUM; PANTHENOL; TRIETHOXYCAPRYLYLSILANE

Sun Bum Signature Clear High Performance Sunscreen Broad Spectrum SPF 50 1.5 OZ

Active Ingredients

Octisalate 5%, Octocrylene 10%, Zinc Oxide 10%

Purpose

Sunscreen

Uses

• helps prevent sunburn • if used as directed with other sun protection measures, (see Directions) decreases the risk of skin cancer and early skin aging caused by the sun

Warnings

For external use only

Do not use on damaged or broken skin

When using this product keep out of eyes. Rinse with water to remove.

Stop use and ask a doctor if rash occurs

Keep out of reach of children. If swallowed, get medical help or contact a Poison Control Center immediately.

Warnings

Keep Out Of Reach Of Children

Directions

• shake well before use

• apply liberally 15 minutes before sun exposure

• reapply: • after 80 minutes of swimming or sweating • immediately after towel drying • at least every 2 hours

• children under 6 months of age: ask a doctor

• Sun Protection Measures. Spending time in the sun increases your risk of skin cancer and early skin aging. To decrease this risk, regularly use a sunscreen with a Broad Spectrum SPF value of 15 or higher and other sun protection measures including:

• limit time in the sun, especially from 10 a.m.- 2 p.m.

• wear long-sleeved shirts, pants, hats and sunglasses

Directions

• shake well before use

• apply liberally 15 minutes before sun exposure

Other Information

protect this product from excessive heat and direct sun

Inactive Ingredients

WATER, C12-15 ALKYL BENZOATE, TRIMETHYLPENTANEDIOL/ADIPIC ACID COPOLYMER, BUTYROSPERMUM PARKII (SHEA) BUTTER, GLYCERIN, POLYESTER-8, ARACHIDYL ALCOHOL, PANTHENOL, ALOE BARBADENSIS LEAF JUICE, TOCOPHEROL ACETATE, SODIUM HYALURONATE, ASCORBYL PALMITATE, BEESWAX, BEHENYL ALCOHOL, ARACHIDYL GLUCOSIDE, SORBITAN OLEATE, SORBITOL, LECITHIN, XANTHAN GUM, OLEIC ACID, GLYCERYL CAPRYLATE, HYDROXYETHYL ACRYLATE/SODIUM ACRYLOYLDIMETHYL TAURATE COPOLYMER, TRIETHOXYCAPRYLYLSILANE, DISODIUM EDTA, PHENOXYETHANOL, CAPRYLYL GLYCOL, ETHYLHEXYLGLYCERIN

Questions?

1-877-978-6286